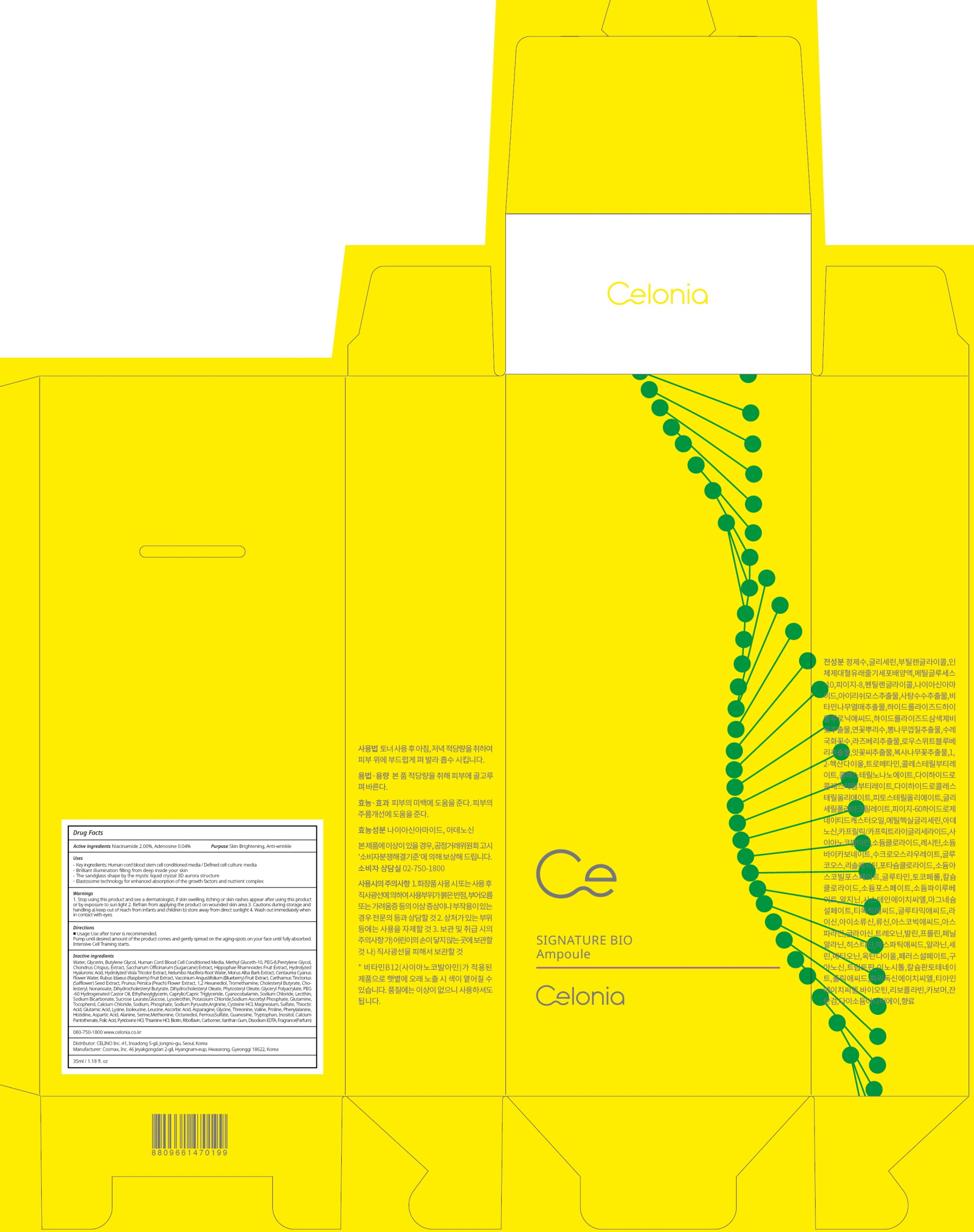 DRUG LABEL: CELONIA SIGNATURE BIO AMPOULE
NDC: 73655-010 | Form: LIQUID
Manufacturer: Celino Inc.
Category: otc | Type: HUMAN OTC DRUG LABEL
Date: 20200310

ACTIVE INGREDIENTS: Niacinamide 0.70 g/35 mL; Adenosine 0.014 g/35 mL
INACTIVE INGREDIENTS: Water; Glycerin

ACTIVE INGREDIENT

Active ingredients: Niacinamide 2.00%, Adenosine 0.04%

INACTIVE INGREDIENT

Inactive ingredients:

Water,Glycerin,Butylene Glycol,Human Cord Blood Cell Conditioned Media,Methyl Gluceth-10,PEG-8,Pentylene Glycol, Chondrus Crispus Extract,Saccharum Officinarum (Sugarcane) Extract,Hippophae Rhamnoides Fruit Extract,Hydrolyzed Hyaluronic Acid,Hydrolyzed Viola Tricolor Extract,Nelumbo Nucifera Root Water,Morus Alba Bark Extract,Centaurea Cyanus Flower Water,Rubus Idaeus (Raspberry) Fruit Extract,Vaccinium Angustifolium (Blueberry) Fruit Extract,Carthamus Tinctorius (Safflower) Seed Extract,Prunus Persica (Peach) Flower Extract,1,2-Hexanediol,Tromethamine,Cholesteryl Butyrate,Cholesteryl Nonanoate,Dihydrocholesteryl Butyrate,Dihydrocholesteryl Oleate,Phytosteryl Oleate,Glyceryl Polyacrylate,PEG-60 Hydrogenated Castor Oil,Ethylhexylglycerin, Caprylic/Capric Triglyceride,Cyanocobalamin,Sodium Chloride,Lecithin,Sodium Bicarbonate,Sucrose Laurate,Glucose,Lysolecithin,Potassium Chloride,Sodium Ascorbyl Phosphate,Glutamine,Tocopherol,Calcium Chloride,Sodium Phosphate,Sodium Pyruvate,Arginine,Cysteine HCl,Magnesium Sulfate,Thioctic Acid,Glutamic Acid,Lysine,Isoleucine,Leucine,Ascorbic Acid,Asparagine,Glycine,Threonine,Valine,Proline,Phenylalanine,Histidine,Aspartic Acid,Alanine,Serine,Methionine,Octanediol,Ferrous Sulfate,Guanosine,Tryptophan,Inositol,Calcium Pantothenate,Folic Acid,Pyridoxine HCl,Thiamine HCl,Biotin,Riboflavin,Carbomer,Xanthan Gum,Disodium EDTA,Fragrance(Parfum)

PURPOSE

Purpose: Skin Brightening, Anti wrinkle

WARNINGS

1. Stop using this product and see a dermatologist, if skin swelling, itching or skin rashes appear after using this product or by exposure to sun light

2. Refrain from applying the product on wounded skin area

3. Cautions during storage and handling a) keep out of reach from infants and children b) store away from direct sunlight

4. Wash out immediately when in contact with eyes

KEEP OUT OF REACH OF CHILDREN

keep out of reach from infants and children

QUESTIONS

080-750-1800

www.celonia.co.kr

Uses

Key ingredients: Human cord blood stem cell conditioned media / Defined cell culture media

Brilliant illumination filling from deep inside your skin

The sandglass shape by the mystic liquid crystal 3D aurora structure

Elastosome technology for enhanced absorption of the growth factors and nutrient complex

Directions

Use after toner is recommended. Pump until desired amount of the product comes and gently spread on the aging-spots on your face until fully absorbed. Intensive Cell Training starts.